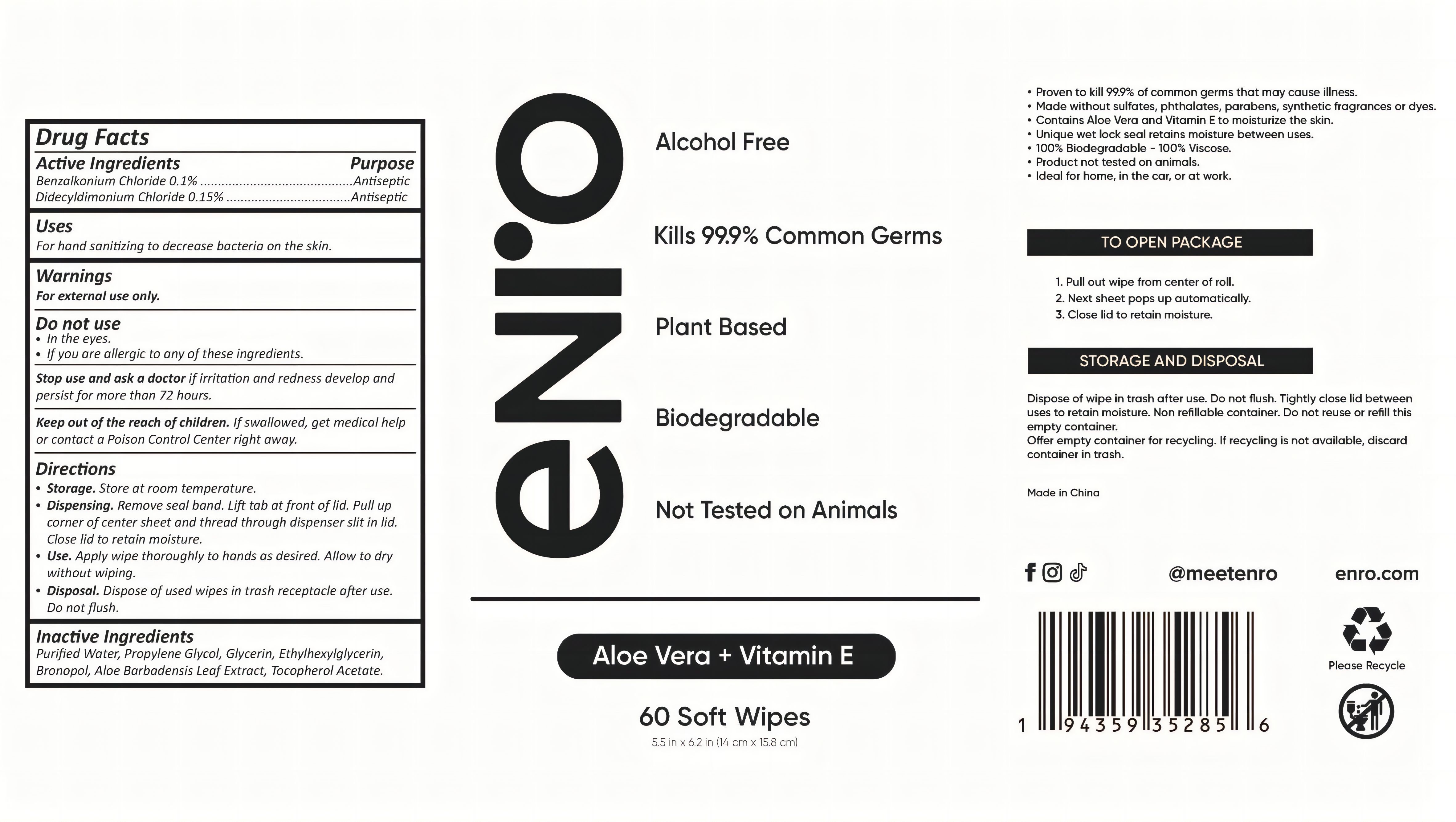 DRUG LABEL: 60 soft wipes
NDC: 75670-011 | Form: CLOTH
Manufacturer: SHANGHAI SANJUN GENERAL MERCHANDISE CO., LTD.
Category: otc | Type: HUMAN OTC DRUG LABEL
Date: 20221210

ACTIVE INGREDIENTS: DIDECYLDIMONIUM CHLORIDE 0.15 g/100 g; BENZALKONIUM CHLORIDE 0.1 g/100 g
INACTIVE INGREDIENTS: WATER; GLYCERIN; ETHYLHEXYLGLYCERIN; BRONOPOL; ALOE VERA LEAF; .ALPHA.-TOCOPHEROL ACETATE; PROPYLENE GLYCOL

75670-011 60 soft wipes Benzalkonium Chloride 0.1% Didecyldimonium Chloride 0.15%

Active Ingredient

Benzalkonium Chloride 0.1 %

Didecyldimonium Chloride 0.15%

PURPOSE

Antiseptic

USE

For hand sanitizing to decrease bacteria on the skin.

Warning

For external use only.
Do not use
In the eyes.
If you are allergic to any of these ingredients.
Stop use and ask a doctor if irritation and redness develop and persist for more than 72 hours.

KEEP OUT OF REACH OF CHILDREN

Keep out of the reach of children. If swallowed, get medical help or contact a Poison Control Center right away.

Directions

Storage. Store at room temperature.
Dispensing. Remove seal band. Lift tab at front of lid. Pull up corner of center sheet and thread through dispenser slit in lid. Close lid to retain moisture.
Use. Apply wipe thoroughly to hands as desired. Allow to dry without wiping.
Disposal. Dispose of used wipes in trash receptacle after use. Do not ﬂush.

Inactive ingredients

Puriﬁed Water, Propylene Glycol, Glycerin, Ethylhexylglycerin, Bronopol, Aloe Barbadensis Leaf Extract, Tocopherol Acetate.